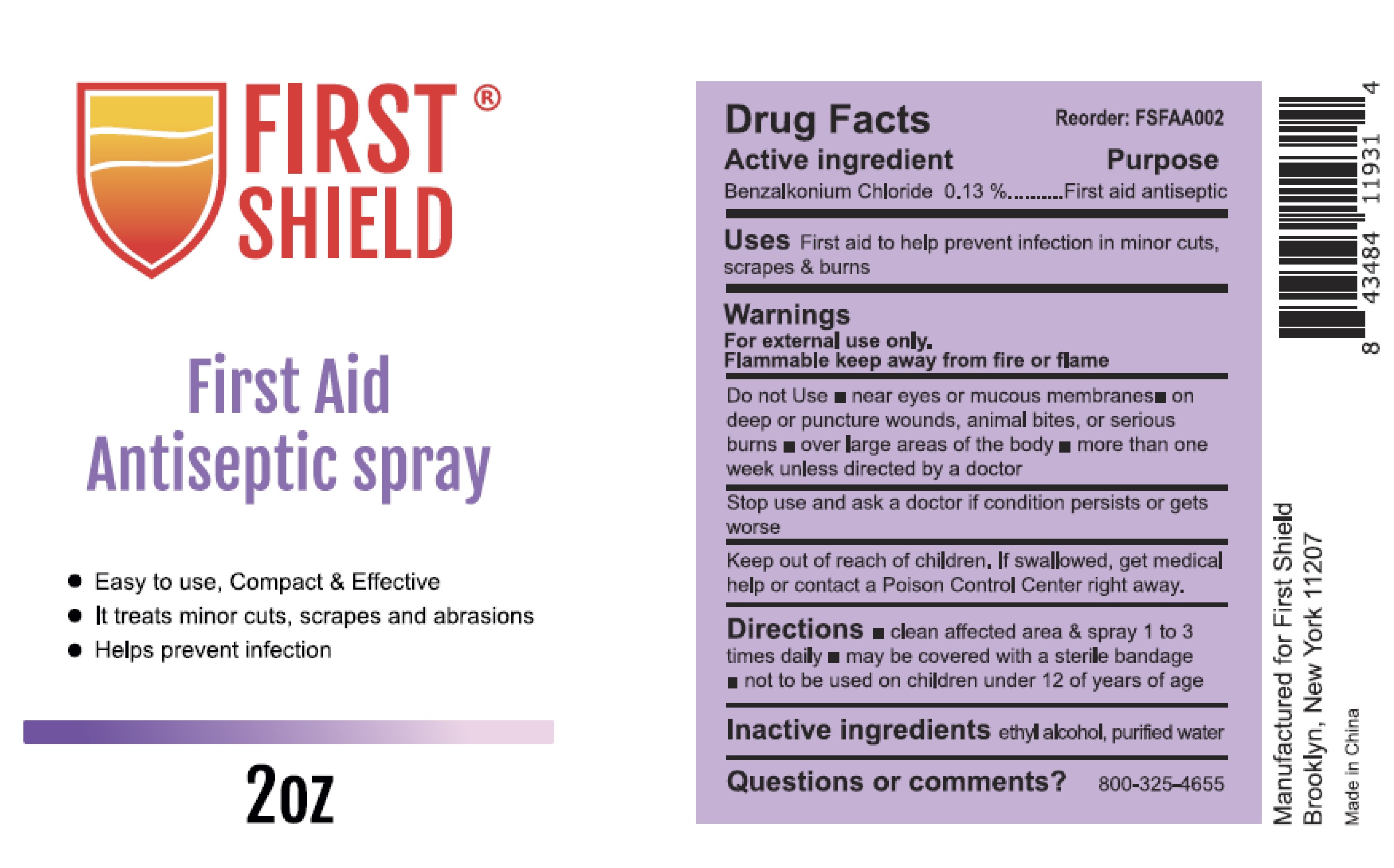 DRUG LABEL: FIRST SHIELD First Aid Antiseptic
NDC: 72976-003 | Form: SPRAY
Manufacturer: Ever Ready First Aid
Category: otc | Type: HUMAN OTC DRUG LABEL
Date: 20240115

ACTIVE INGREDIENTS: BENZALKONIUM CHLORIDE 0.13 g/100 mL
INACTIVE INGREDIENTS: WATER; ALCOHOL

72976-003 FIRST SHIELD
First Aid Antiseptic spray

Active ingredient

Benzalkonium chloride 0.13%

Purpose

First aid antiseptic

Uses

First aid to help prevent infection in minor cuts, scrapes & burns

Warnings

For external use only

Flammable keep away from fire or flame

Do not use* near eyes or mucous membranes *on deep or puncture wounds , animal bites, or serious burns *over large areas of the body* more than one week unless directed by a doctor

Stop use and ask a doctor if condition persists or gets worse

Keep out of reach of children. If swallowed, get medical help or contact a Poison Control Center right away.

Directions

- clean affected area & spray 1 to 3 times daily
- may be covered with a sterile bandage
- not to be used on children under 12 of years of age.

Inactive ingredients ethyl alcohol, purified water

Questions or comments？ 800-325-4655